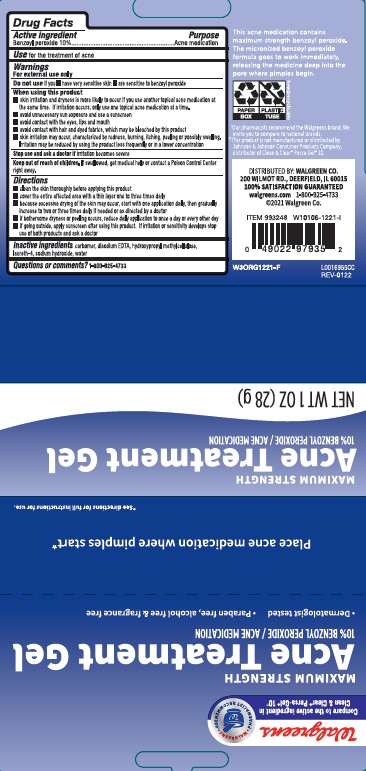 DRUG LABEL: Acne Treatment
NDC: 0363-0229 | Form: GEL
Manufacturer: Walgreen Co.
Category: otc | Type: HUMAN OTC DRUG LABEL
Date: 20260212

ACTIVE INGREDIENTS: BENZOYL PEROXIDE 1 mg/1 g
INACTIVE INGREDIENTS: CARBOMER INTERPOLYMER TYPE A (ALLYL SUCROSE CROSSLINKED); EDETATE DISODIUM; HYPROMELLOSES; LAURETH-4; SODIUM HYDROXIDE; WATER

Walgreens 229.001/229AC-AD
10% Benzoyl Peroxide Acne Medicated Gel

Active ingredient

Benzoyl peroxide 10%

Purpose

Acne medication

Use

for the treatment of acne

Warnings

For external use only

Do not use if you

- have very sensitive skin
- are sensitive to benzoyl peroxide

When using this product

- skin irritation and dryness is more likely to occur if you use aother topical acne medication at the same time. If irritation occurs, only use one topical acne medication at a time
- avoid unnecessary sun exposure and use a sunscreen
- avoid contact with eyes, lips and mouth
- avoid contact with hair and dyed fabrics, which may be bleached by this product
- skin irritation may occur, characterized by redness, burning, itching, peeling or possible swelling. Irritation may be reduced by using the product less frequently or in a lower concentration

Stop use and ask a doctor if

irritation becomes severe

Keep out of reach of children.

If swallowed, get medical help or contact a Poison Control Center right away.

Directions

- clean the skin thoroughly before applying this product
- cover the entire affected area with a thin layer one to three times daily
- because excessive drying of the skin may occur, start with one application daily, then gradually increase to two or three times daily if needed or as directed by a doctor
- if bothersome dryness or peeling occurs, reduce daily application to once a day or every other day
- if going outside, apply sunscreen after using this product. If irritation or sensitivity develops stop use of both products and ask a doctor

Inactive ingredients

carbomer, disodium EDTA, hydroxypropyl methylcellulose, laureth-4, sodium hydroxide, water

Questions or comments?

1-800-925-4733

Claims

This acne medication contains maximum strength benzoyl peroxide. The micronized benzoyl peroxide formula goes to work immediately, releasing the medicine deep into the pore where pimples begin.

Our pharmacists recommend the Walgreens brand. We invite you to compare to national brands.

Disclaimer

††This product is not manufactured or distributed by Johnson & Johnson Consumer Products Company, distributor of Clean & Clear®Persa-Gel®10.

ADVERSE REACTION

Distributed by Walgreen Co.

200 Wilmot Rd., Deerfield, IL 600015

walgreens.com 1-800-925-4733

©2021 Walgreen Co.

PAPER BOX

PLASTIC TUBE

how2recycle.info

princpal display panel

Walgreens

WALGREENS PHARMACIST RECOMMENDED

Compare to the active ingredient in Clean & Clear®Persa-Gel®10††

Maximum Strength

Acne Treatment Gel

10% benzoyl peroxide/acne medication

- Dermatologist tested
- Paraben free, alcohol free & fragrance free

NET WT 1 OZ (28 g)

Place acne medication where pimples start*

*See directions for full instructions for use.

Maximum Strength

Acne Treatment Gel

10% benzoyl peroxide/acne medication

NET WT 1 OZ (28 g)